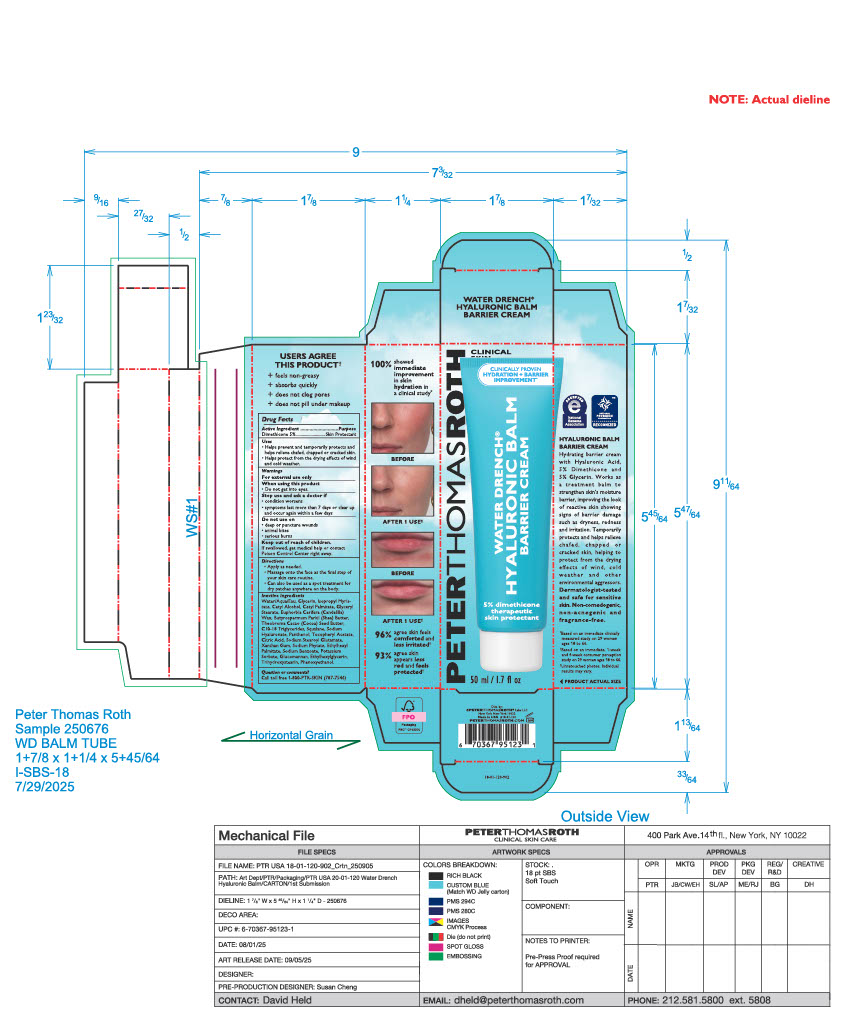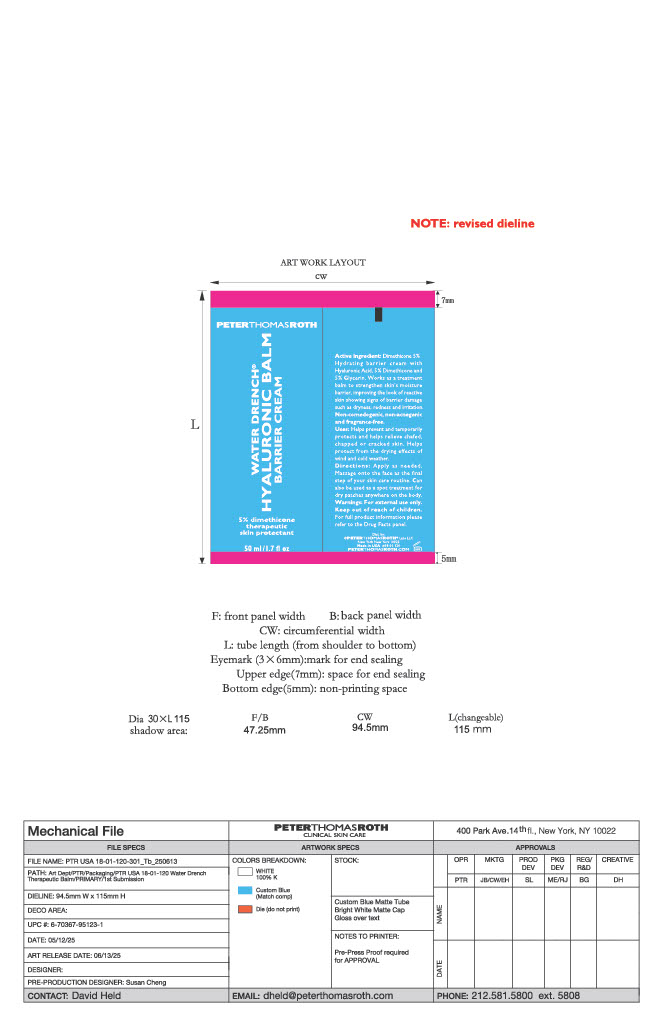 DRUG LABEL: Water Drench Hyaluronic Healing Balm
NDC: 54031-581 | Form: CREAM
Manufacturer: Peter Thomas Roth Labs, LLC
Category: otc | Type: HUMAN OTC DRUG LABEL
Date: 20260113

ACTIVE INGREDIENTS: DIMETHICONE 2.41 g/48.19 g
INACTIVE INGREDIENTS: CITRIC ACID; C10-18 TRIGLYCERIDES; PANTHENOL; ETHYLHEXYL PALMITATE; GLYCERYL STEARATE; ISOPROPYL MYRISTATE; CETYL PALMITATE; SODIUM BENZOATE; GLYCERIN; CETYL ALCOHOL; SODIUM HYALURONATE; ALPHA-TOCOPHEROL ACETATE; SODIUM PHYTATE; GLUCOMANNAN; TRIHYDROXYSTEARIN; ETHYLHEXYLGLYCERIN; PHENOXYETHANOL; EUPHORBIA CERIFERA (CANDELILLA) WAX; BUTYROSPERMUM PARKII (SHEA) BUTTER; XANTHAN GUM; SODIUM STEAROYL GLUTAMATE; SQUALANE; WATER; THEOBROMA CACAO (COCOA) SEED BUTTER; POTASSIUM SORBATE

PTR - Water Drench Hyaluronic Healing Balm (OTC)
Formula: XYL1-136 Rev. 1

ACTIVE INGREDIENT

Dimethicone 5%

PURPOSE

Skin protectant

Uses

- Helps prevent and temporarily protects and helps relieve chafed, chapped or cracked skin.
- Helps protect from the drying effects of wind and cold weather.

Uses

Helps prevent and temporarily protects and helps relieve chafed, chapped or cracked skin.
Helps protect from the drying effects of wind and cold weather.

WARNINGS

For external use only

WHEN USING

- Do not get into eyes

Stop use and ask a doctor if

- Condition worsens
- Symptoms last more than 7 days or clear up and occur again within a few days

Do not use on

- deep or pumcture wounds
- animal bites
- serious burns

KEEP OUT OF REACH OF CHILDREN

If swallowed, get medical help or contact Poison Control Center right away.

Directions

- Apply as needed
- Massage onto the face as the final step of your skin care routine.
- Can also be used as a spot treatment for dry patches anywhere on the body.

INACTIVE INGREDIENT

WATER/AQUA/EAU, GLYCERIN, ISOPROPYL MYRISTATE, CETYL ALCOHOL, CETYL PALMITATE, GLYCERYL STEARATE, EUPHORBIA CERIFERA (CANDELILLA) WAX, BUTYROSPERMUM PARKII (SHEA) BUTTER, THEOBROMA CACAO (COCOA) SEED BUTTER, C10-18 TRIGLYCERIDES, SQUALANE, SODIUM HYALURONATE, PANTHENOL, TOCOPHERYL ACETATE, CITRIC ACID, SODIUM STEAROYL GLUTAMATE, XANTHAN GUM, SODIUM PHYTATE, ETHYLHEXYL PALMITATE, SODIUM BENZOATE, POTASSIUM SORBATE, GLUCOMANNAN, ETHYLHEXYLGLYCERIN, TRIHYDROXYSTEARIN, PHENOXYETHANOL

QUESTIONS

Question or comments?

Cal tl free 1-800-PTR-SKIN (787-7546)